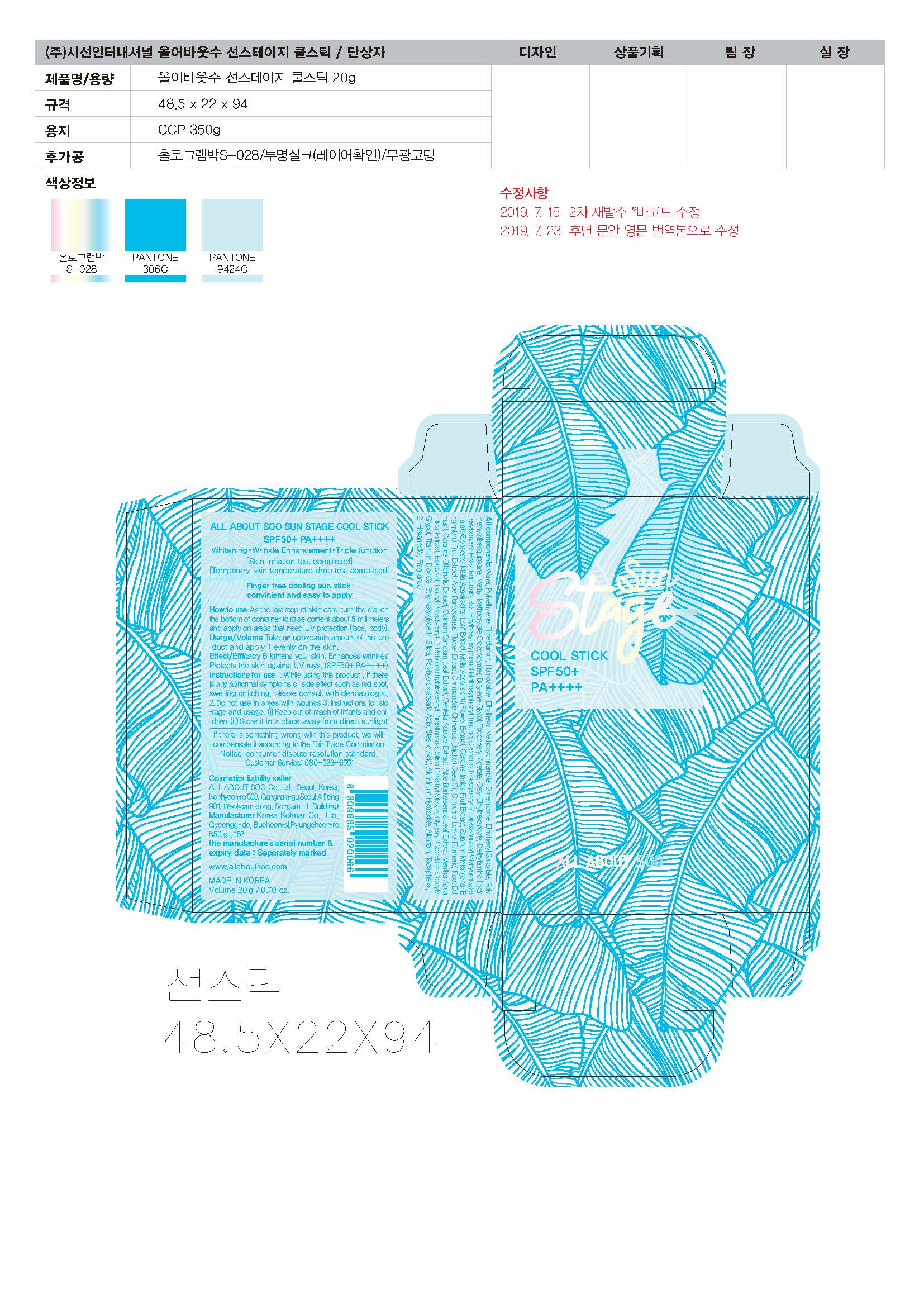 DRUG LABEL: ALL ABOUT SOO SUN STAGE COOLSTICK SPF50 PA
NDC: 73329-0001 | Form: STICK
Manufacturer: ALL ABOUT SOO
Category: otc | Type: HUMAN OTC DRUG LABEL
Date: 20190903

ACTIVE INGREDIENTS: TITANIUM DIOXIDE 0.234 g/100 g
INACTIVE INGREDIENTS: WATER; BUTYLENE GLYCOL; DIMETHICONE

Drug Facts

ACTIVE INGREDIENT

Titanium Dioxide

INACTIVE INGREDIENT

WATER
POLYETHYLENE
TRIHEPTANOIN
HOMOSALATE
ETHYLHEXYL METHOXYCINNAMATE
BHT
DIMETHICONE
ETHYLHEXYL SALICYLATE
POLYMETHYLSILSESQUIOXANE
METHYL METHACRYLATE CROSSPOLYMER
BUTYLENE GLYCOL
CETYL ETHYLHEXANOATE
SILICA DIMETHYL SILYLATE
POLYMETHYLSILSESQUIOXANE
SILICA
POLYHYDROXYSTEARIC ACID
TOCOPHERYL ACETATE
BIS-ETHYLHEXYLOXYPHENOL METHOXYPHENYL TRIAZINE
DIETHYLAMINO HYDROXYBENZOYL HEXYL BENZOATE
POLYGLYCERYL-4 DIISOSTEARATE/POLYHYDROXYSTEARATE/SEBACATE
OZOKERITE
DIMETHICONE
BISABOLOL
LAURYL POLYGLYCERYL-3 POLYDIMETHYLSILOXYETHYL DIMETHICONE
TOCOPHEROL
FRAGRANCE
CAPRYLYL GLYCOL
STEARIC ACID
ALUMINUM HYDROXIDE
GLYCERYL CAPRYLATE
MELIA AZADIRACHTA LEAF EXTRACT
MELIA AZADIRACHTA FLOWER EXTRACT
COCCINIA INDICA FRUIT EXTRACT
SOLANUM MELONGENA (EGGPLANT) FRUIT EXTRACT
ALOE BARBADENSIS FLOWER EXTRACT
SIMMONDSIA CHINENSIS (JOJOBA) SEED OIL
OCIMUM SANCTUM LEAF EXTRACT
CORALLINA OFFICINALIS EXTRACT
CURCUMA LONGA (TURMERIC) ROOT EXTRACT
ETHYLHEXYLGLYCERIN
TOCOPHEROL
ALLANTOIN
WATER
BUTYLENE GLYCOL
ALOE BARBADENSIS LEAF EXTRACT
PENTYLENE GLYCOL
1,2-HEXANEDIOL
CAPRYLYL GLYCOL
WATER
PENTYLENE GLYCOL
CENTELLA ASIATICA EXTRACT
ETHYLHEXYLGLYCERIN
WATER
1,2-HEXANEDIOL
WATER
DIPROPYLENE GLYCOL
1,2-HEXANEDIOL
MENTHA AQUATICA EXTRACT

PURPOSE

Brightens your skin. Enhances wrinkles Protects the skin against UV rays. (SPF50+,PA++++)

keep out of reach of the children

INDICATIONS AND USAGE

As the last step of skin care, turn the dial on
the bottom of container to raise content about 5 millimeters
and apply on areas that need UV protection (face, body).
Usage/Volume Take an appropriate amount of this pro
-duct and apply it evenly on the skin.

WARNINGS

1. While using this product , if there
is any abnormal symptoms or side effect such as red spot,
swelling or itching, please consult with dermatologist.
2. Do not use in areas with wounds 3. Instructions for sto
-rage and usage. (i) Keep out of reach of infants and chil
-dren (ii) Store it in a place away from direct sunlight

DOSAGE AND ADMINISTRATION

for external use only